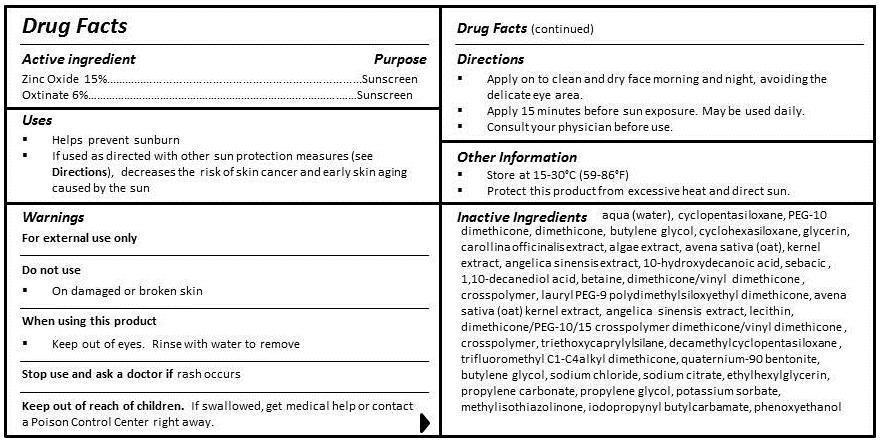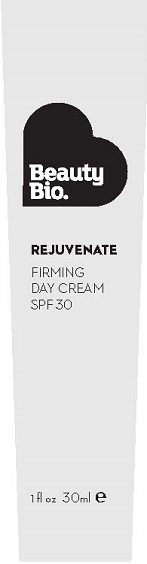 DRUG LABEL: FIRMING DAY
NDC: 54272-202 | Form: CREAM
Manufacturer: CEN BEAUTY LLC
Category: otc | Type: HUMAN OTC DRUG LABEL
Date: 20130304

ACTIVE INGREDIENTS: ZINC OXIDE 15 g/100 mL; OCTINOXATE 6 g/100 mL
INACTIVE INGREDIENTS: WATER; CYCLOMETHICONE 5; PEG-10 DIMETHICONE (600 CST); DIMETHICONE; BUTYLENE GLYCOL; CYCLOMETHICONE 6; GLYCERIN; CORALLINA OFFICINALIS; PORPHYRA UMBILICALIS; OAT; ANGELICA SINENSIS WHOLE; 10-HYDROXYDECANOIC ACID; SEBACIC ACID; 1,10-DECANEDIOL; BETAINE; DIMETHICONE/VINYL DIMETHICONE CROSSPOLYMER (SOFT PARTICLE); LECITHIN, SOYBEAN; PEG-9 POLYDIMETHYLSILOXYETHYL DIMETHICONE; DIMETHICONE PEG-10 PHOSPHATE; TRIETHOXYCAPRYLYLSILANE; DODECAMETHYLPENTASILOXANE; 2,2,2-TRIFLUOROACETOPHENONE; QUATERNIUM-91; BENTONITE; BUTYLENE GLYCOL; SODIUM CHLORIDE; ETHYLHEXYLGLYCERIN; SODIUM CITRATE; PROPYLENE CARBONATE; PROPYLENE GLYCOL; POTASSIUM SORBATE; METHYLISOTHIAZOLINONE; IODOPROPYNYL BUTYLCARBAMATE; PHENOXYETHANOL

ACTIVE INGREDIENT

ZINC OXIDE 15%

OCTINOXATE 6%

PURPOSE

SUNSCREEN

USES

- Helps prevent sunburn
- If used as directed with other sun protection measures (see Directions), decreases the risk of skin cancer and early skin aging caused by the sun

WARNINGS

FOR EXTERNAL USE ONLY

DO NOT USE

- On damaged or broken skin

WHEN USING THIS PRODUCT

- Keep out of eyes. Rinse with water to remove.

STOP USE AND ASK A DOCTOR IF RASH OCCURS.

KEEP OUT OF REACH OF CHILDREN. IF SWALLOWED, GET MEDICAL HELP OR CONTACT A POISON CONTROL CENTER RIGHT AWAY.

DIRECTIONS

- Apply on to clean and dry face morning and night, avoiding the delicate eye area.
- Apply 15 minutes before sun exposure. May be used daily.
- Consult your physician before use.

Other Information

- STORE AT 15-30°C (59-86°F)
- PROTECT THIS PRODUCT FROM EXCESSIVE HEAT AND DIRECT SUN.

INACTIVE INGREDIENT

INGREDIENTS

aqua (water), cyclopentasiloxane, PEG-10 dimethicone, dimethicone, butylene glycol, cyclohexasiloxane, glycerin, carollina officinalis extract, algae extract, avena sativa (oat) kernel extract, angelica sinensis extract, 10-hydroxydecanoic acid, sebacic acid, 1,10-decanediol acid, betaine, dimethicone/vinyl dimethicone crosspolymer, lauryl PEG-9 polydimethylsiloxyethyl dimethicone, lecithin, dimethicone/PEG-10/15 crosspolymer, triethoxycaprylylsilane, decamethylcyclopentasiloxane, trifluoromethyl C1-C4 alkyl dimethicone, quaternium-90, bentonite, butylene glycol, sodium chloride, sodium citrate, ethylhexylglycerin, propylene carbonate, propylene glycol, potassium sorbate, methylisothiazolinone, iodopropynyl butylcarbamate, phenoxyethanol